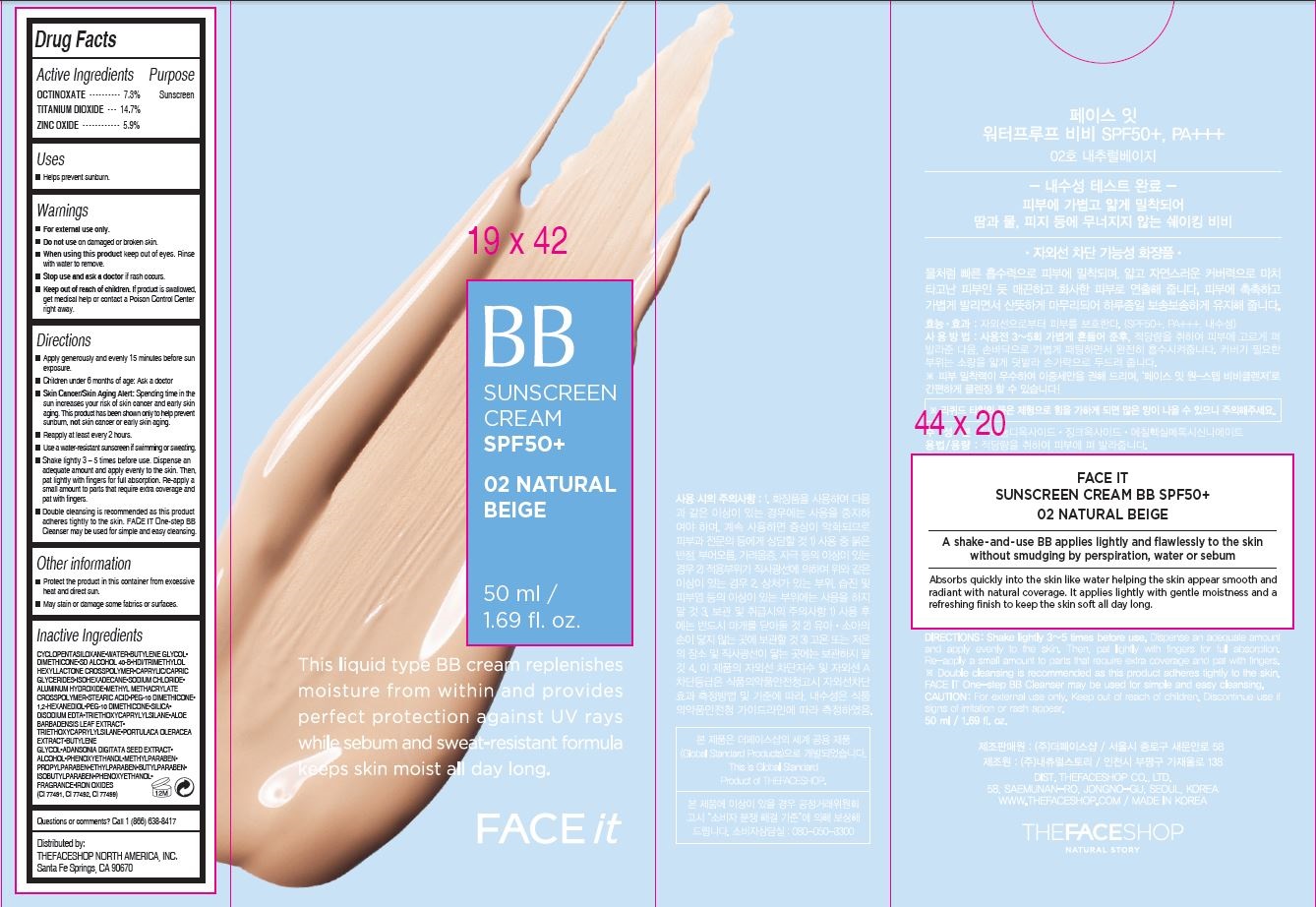 DRUG LABEL: FACE IT BB (Natural Beige)
NDC: 51523-379 | Form: CREAM
Manufacturer: THEFACESHOP CO., LTD.
Category: otc | Type: HUMAN OTC DRUG LABEL
Date: 20141120

ACTIVE INGREDIENTS: ZINC OXIDE 2.95 g/50 mL; OCTINOXATE 3.65 g/50 mL; TITANIUM DIOXIDE 7.35 g/50 mL
INACTIVE INGREDIENTS: WATER

Face It (Natural Beige) 32800379

Active Ingredients

OCTINOXATE • • • • • • • • • • 7.3%

TITANIUM DIOXIDE • • • • •• 14.7%

ZINC OXIDE • • • • • • • • • • • 5.9%

Pupose

Sunscreen

Sunscreen

Sunscreen

Uses

Helps prevent sunburn.

Warnings

For external use only.

Do not use on damaged or broken skin.

When using this product keep out of eyes.

Rinse with water to remove.

Stop use and ask a doctor if rash occurs.

Keep out of reach of children. If product is swallowed,

get medical help or contact a Poison Control Center

right away.

Directions

Apply generously and evenly 15 minutes before sun

exposure.

Children under 6 months of age: Ask a doctor

Skin Cancer/Skin Aging Alert: Spending time in the

sun increases your risk of skin cancer and early skin

aging. This product has been shown only to help prevent

sunburn, not skin cancer or early skin aging.

Reapply at least every 2 hours.

Use a water-resistant sunscreen if swimming or sweating.

Shake lightly 3 – 5 times before use. Dispe nse an

adequate amount and apply evenly to the skin. Then,

pat lightly with fingers for full absorption. Re-apply a

small amount to parts that require extra coverage and

pat with fingers.

Double cleansing is recommended as this product

adheres tightly to the skin. FACE IT One-step BB

Cleanser may be used for simple and easy cleansing.

Other information

Protect the product in this container from excessive heat and direct sun.

May stain or damage some fabrics or surfaces.

Inactive Ingredients

CYCLOPENTASILOXANE•WATER•BUTYLENE GLYCOL•

DIMETHICONE•SD ALCOHOL 40-B•HDI/TRIMETHYLOL

HEXYLLACTONE CROSSPOLYMER•CAPRYLIC/CAPRIC

GLYCERIDES•ISOHEXADECANE•SODIUM CHLORIDE•

ALUMINUM HYDROXIDE•METHYL METHACRYLATE

CROSSPOLYMER•STEARIC ACID•PEG-10 DIMETHICONE•

1,2-HEXANEDIOL•PEG-10 DIMETHICONE•SILICA•

DISODIUM EDTA•TRIETHOXYCAPRYLYLSILANE•ALOE

BARBADENSIS LEAF EXTRACT•

TRIETHOXYCAPRYLYLSILANE•PORTULACA OLERACEA

EXTRACT•BUTYLENE

GLYCOL•ADANSONIA DIGITATA SEED EXTRACT•

ALCOHOL•PHENOXYETHANOL•METHYLPARABEN•

PROPYLPARABEN•ETHYLPARABEN•BUTYLPARABEN•

ISOBUTYLPARABEN•PHENOXYETHANOL•

FRAGRANCE•IRON OXIDES

(CI 77491, CI 77492, CI 77499)

Questions

Questions or comments? Call 1 (866) 638-8417

Distributed by:

THEFACESHOP NORTH AMERICA, INC.

Santa Fe Springs, CA 90670

PACKAGE LABEL

FACE it

BB SUNSCREEN CREAM SPF50+

02 NATURAL BEIGE

This liquid type BB cream replenishes

moisture from within and provides

perfect protection agains UV rays

while sebum and sweat-resistant formula

keeps skin moist all day long.